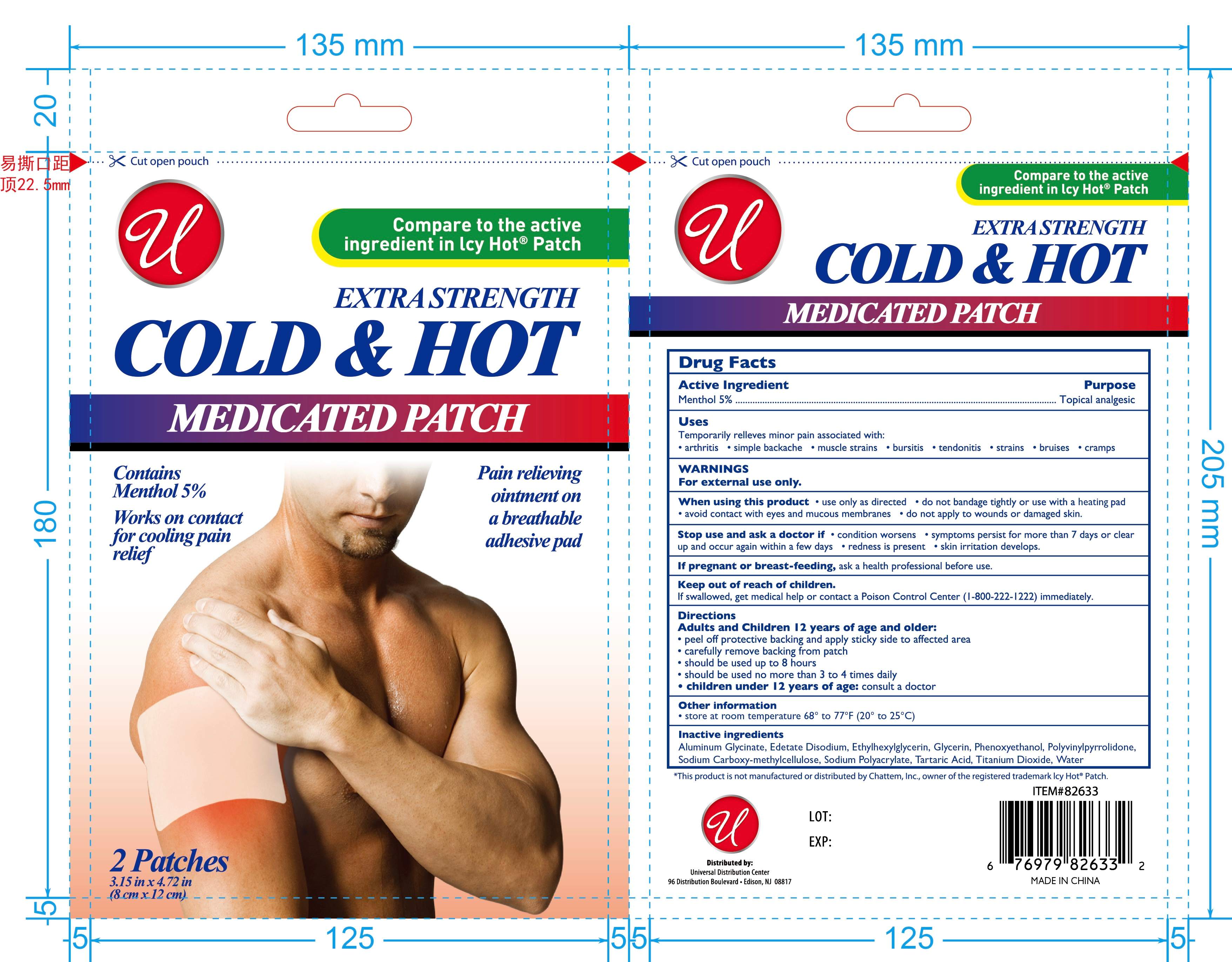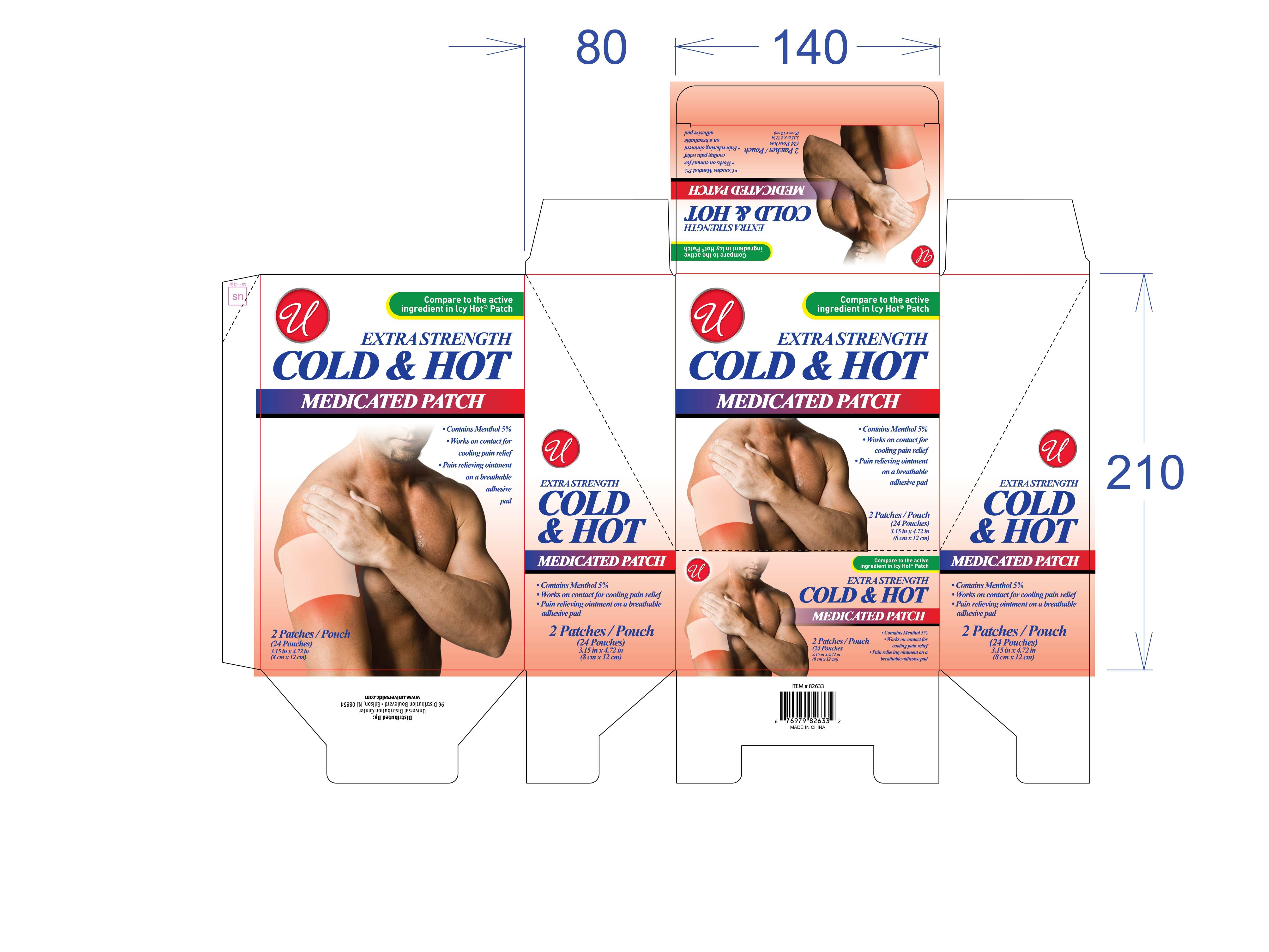 DRUG LABEL: COLD AND HOT MEDICATED Patch
NDC: 83559-014 | Form: PATCH
Manufacturer: Henan Enokon Medical Instrument Co., Ltd.
Category: otc | Type: HUMAN OTC DRUG LABEL
Date: 20260131

ACTIVE INGREDIENTS: MENTHOL 5 g/100 1
INACTIVE INGREDIENTS: ETHYLHEXYLGLYCERIN; CARBOXYMETHYLCELLULOSE SODIUM, UNSPECIFIED; TARTARIC ACID; TITANIUM DIOXIDE; WATER; PHENOXYETHANOL; EDETATE DISODIUM; SODIUM POLYACRYLATE (2500000 MW); GLYCERIN; POVIDONE, UNSPECIFIED; DIHYDROXYALUMINUM AMINOACETATE ANHYDROUS

83559-014

Active Ingredient

Menthol 5%

Purpose

Topical analgesic

Use

Temporarily relieve minor pain associated with:
• arthritis • simple backache • muscle strains • bursitis • tendonitis • strains • bruises • cramps

Warnings

For external use only.

When Using

When using this product • use only as directed • do not bandage tightly or use with a heating pad
• avoid contact with eyes and mucous membranes • do not apply to wounds or damaged skin.

Stop Use

Stop use and ask a doctor if • condition worsens • symptoms persist for more than 7 days or clear up and occur again within a few days • redness is present • skin irritation develops.

Ask Doctor

If pregnant or breast-feeding, ask a health professional before use.

Keep Out Of Reach Of Children

If swallowed, get medical help or contact a Poison Control Center (1-800-222-1222) immediately.

Directions

Adults and Children 12 years of age and older:
• peel off protective backing and apply sticky side to affected area
• carefully remove backing from patch
• should be used up to 8 hours
• should be used no more than 3 to 4 times daily
• children under 12 years of age: consult a doctor

Other information

• store at room temperature 68° to 77°F (20° to 25°C)

Compare to the active ingredient in Icy Hot® Patch

EXTRA STRENGTH

Contains Menthol 5%

Works on contact for cooling pain relief

Pain relieving ointment on a breathable adhesive pad

*This product is not manufactured or distributed by Chattem Inc., owner of the registered trademark Icy Hot® Patch.

Distributed by:

Universal Distribution Center
96 Distribution Boulevard • Edison, NJ 08817

MADE IN CHINA

www.universaldc.com

Inactive ingredients

Aluminum Glycinate, Edetate Disodium, Ethylhexylglycerin, Glycerin, Phenoxyethanol, Polyvinylpyrrolidone, Sodium Carboxy-methylcellulose, Sodium Polyacrylate, Tartaric Acid, Titanium Dioxide, Water

Questions

www.universaldc.com